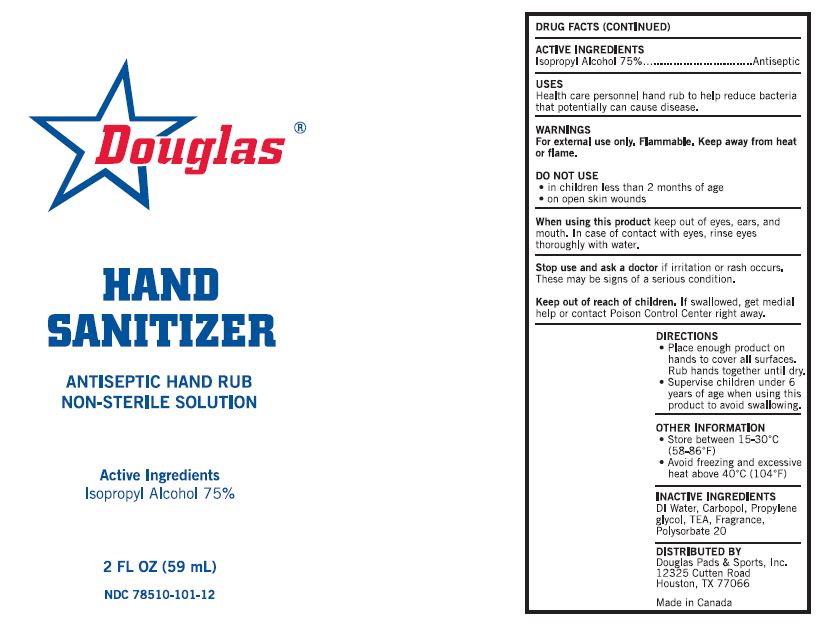 DRUG LABEL: DOUGLAS - HAND SANITIZER
NDC: 78510-101 | Form: GEL
Manufacturer: Douglas Pads & Sports, Inc
Category: otc | Type: HUMAN OTC DRUG LABEL
Date: 20200603

ACTIVE INGREDIENTS: ISOPROPYL ALCOHOL 75 mL/100 mL
INACTIVE INGREDIENTS: WATER; CARBOMER HOMOPOLYMER, UNSPECIFIED TYPE; PROPYLENE GLYCOL; TROLAMINE; POLYSORBATE 20

Douglas

ACTIVE INGREDIENT

ISOPROPYL ALCOHOL 75%

PURPOSE

ANTISEPTIC

USES

HEALTH CARE PERSONNEL HAND RUB TO HELP REDUCE BACTERIA THAT POTENTIALLY CAN CAUSE DISEASE.

WARNINGS

FOR EXTERNAL USE ONLY.

FLAMMABLE, KEEP AWAY FROM HEAT OR FLAME.

DO NOT USE

- IN CHILDREN LESS THAN 2 MONTHS OF AGE
- ON OPEN SKIN WOUNDS

WHEN USING THIS PRODUCT KEEP OUT OF EYES, EARS, AND MOUTH. IN CASE OF CONTACT WITH EYES, RINSE EYES THOROUGHLY WITH WATER.

STOP USE AND ASK A DOCTOR IF IRRITATION OR RASH OCCURS. THESE MAY BE SIGNS OF A SERIOUS CONDITION.

KEEP OUT OF REACH OF CHILDREN. IF SWALLOWED, GET MEDICAL HELP OR CONTACT A POISON CONTROL CENTER RIGHT AWAY.

DIRECTIONS

- PLACE ENOUGH PRODUCT ON HANDS TO COVER ALL SURFACES. RUB HANDS TOGETHER UNTIL DRY.
- SUPERVISE CHILDREN UNDER 6 YEARS OF AGE WHEN USING THIS PRODUCT TO AVOID SWALLOWING.

OTHER INFORMATION

- STORE BETWEEN 15-30°C (58-86°F)
- AVOID FREEZING AND EXCESSIVE HEAT ABOVE 40°C (104°F)

INACTIVE INGREDIENTS

DI WATER, CARBOPOL, PROPYLENE GLYCOL, TEA, FRAGRANCE, POLYSORBATE 20